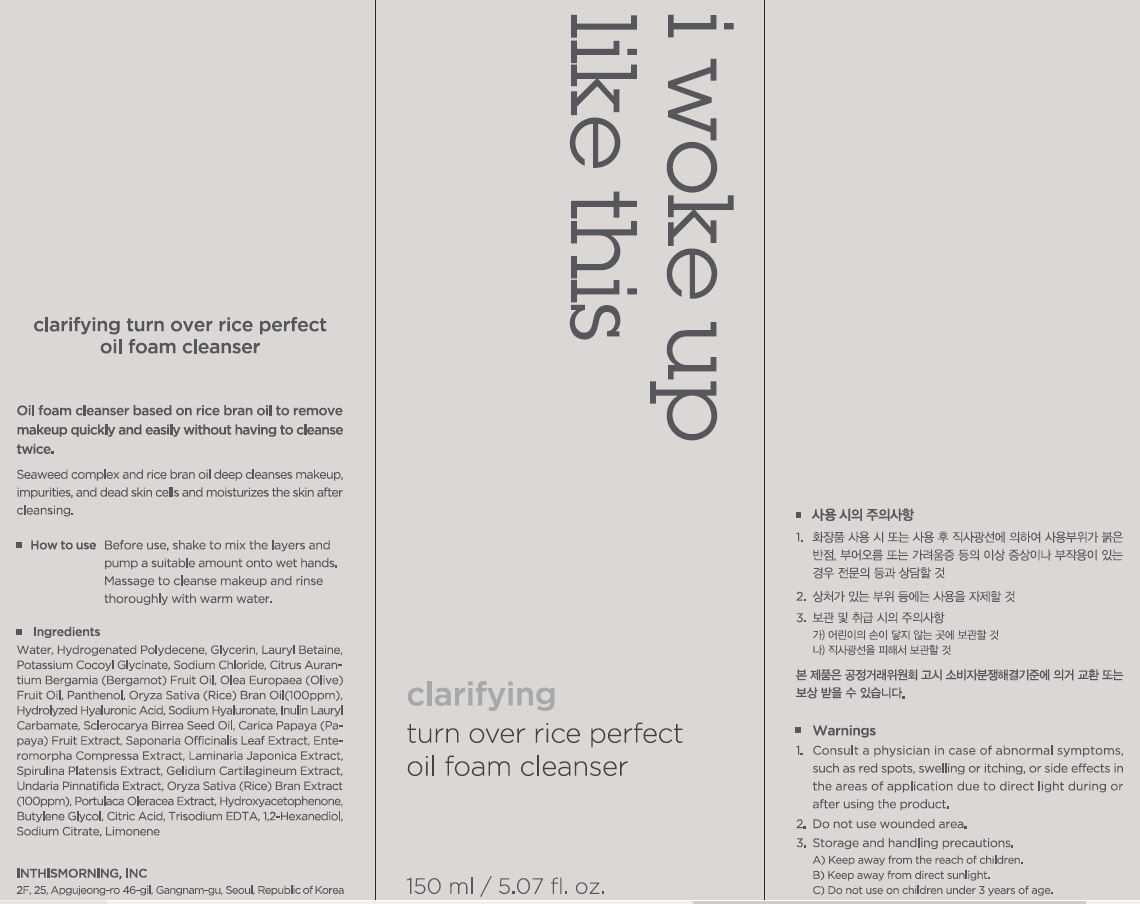 DRUG LABEL: Claritying turn over rice perfect oil foam cleanser
NDC: 71217-0064 | Form: LIQUID
Manufacturer: inthismorning co ltd
Category: otc | Type: HUMAN OTC DRUG LABEL
Date: 20230201

ACTIVE INGREDIENTS: RICE BRAN OIL 0.01 g/100 mL
INACTIVE INGREDIENTS: WATER; GLYCERIN

Drug Facts

ACTIVE INGREDIENT

rice bran oil

INACTIVE INGREDIENT

Water, Glycerin, etc

PURPOSE

to remove makeup quickly and easily without having no cleanse twice

keep out or reach of the children

INDICATIONS AND USAGE

before use, shake to mix the layers and pump a suitable amount onto wet hands,

massage to cleanse makeup and rinse thoroughly with warm water

WARNINGS

This product is for exeternal use only. Do not use for internal use
Storage and handling precautions
If possible, avoid direct sunlight and store in cool and area of low humidity in order to maintain the quality of the product and avoid misuse
Avoid placing the product near fire and store out in reach of children

- consult a physician in case of abnormal symptoms, such as red spots, swelling or itching, or side effects in the areas of application due to direct light during or after using the product

- do not use on wounded area

DOSAGE AND ADMINISTRATION

for external use only